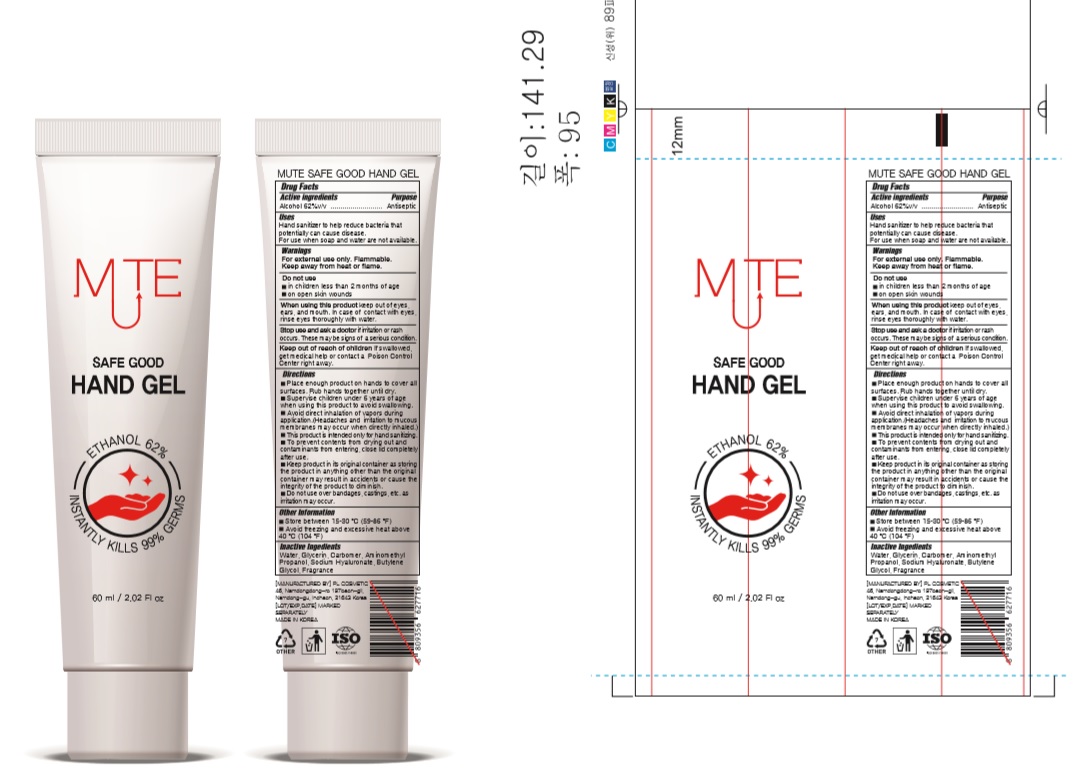 DRUG LABEL: SAFE GOOD HAND Gel
NDC: 74339-9662 | Form: GEL
Manufacturer: PL COSMETIC
Category: otc | Type: HUMAN OTC DRUG LABEL
Date: 20200618

ACTIVE INGREDIENTS: ALCOHOL 37.2 mL/60 mL
INACTIVE INGREDIENTS: GLYCERIN; CARBOMER HOMOPOLYMER, UNSPECIFIED TYPE; WATER; BUTYLENE GLYCOL; HYALURONATE SODIUM; AMINOMETHYLPROPANOL

[SAFE GOOD HAND Gel] 60 ml : 74339-9662